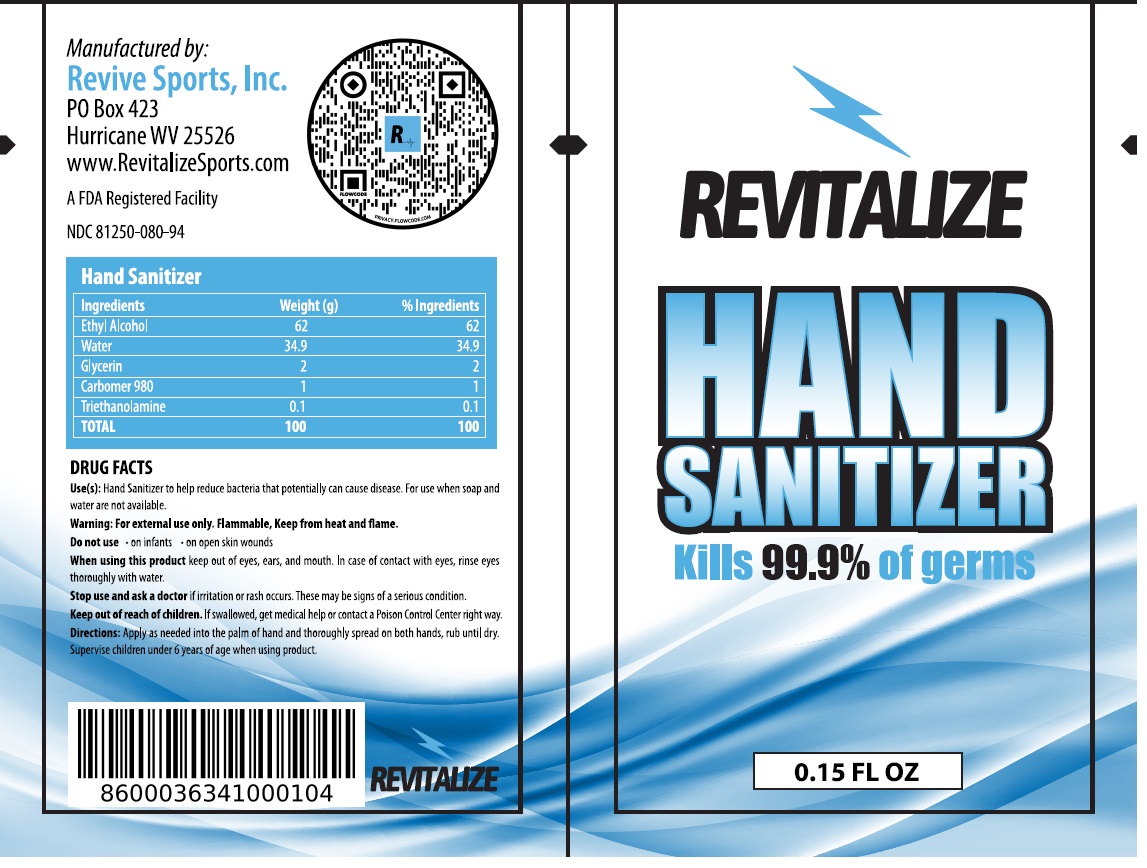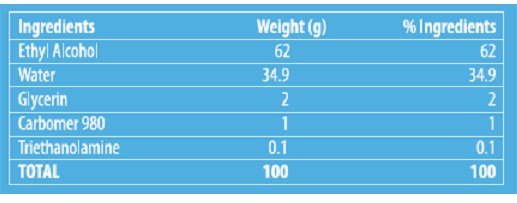 DRUG LABEL: Revitalize Sports Hand Sanitizer
NDC: 81250-080 | Form: GEL
Manufacturer: Revive Sports Inc.
Category: otc | Type: HUMAN OTC DRUG LABEL
Date: 20201218

ACTIVE INGREDIENTS: ALCOHOL 62 mL/100 mL
INACTIVE INGREDIENTS: WATER; GLYCERIN; CARBOMER HOMOPOLYMER TYPE C (ALLYL PENTAERYTHRITOL CROSSLINKED); TROLAMINE

REVITALIZE HAND SANITIZER

Active ingredient:

Ethyl Alcohol 62%

Purpose

Antiseptic

Use(s):

Hand Sanitizer to help reduce bacteria that potentially can cause disease For use when soap and water are not available.

Warning:

For external use only. Flammable, Keep from heat and flame.

Do not use • on infants • on open skin wounds

When using this product keep out of eyes, ears, and mouth. In case of contact with eyes, rinse eyes thoroughly with water.

Stop use and ask a doctor if irritation or rash occurs. These maybe signs of a serious condition.

Keep out of reach of children. If swallowed, get medical help or contact a Poison Control Center right away.

Directions:

Apply as needed into the palm of hand and thoroughly spread on both hands, rub until dry. Supervise children under 6 years of age when using product.

Ingredients

Water, Glycerin, Carbomer 980, Triethanolamine

Kills 99.9% of germs

Manufactured by:

Revive Sports, Inc.
PO Box 423
Hurricane WV 25526
www.RevitalizeSports.com

A FDA Registered Facility